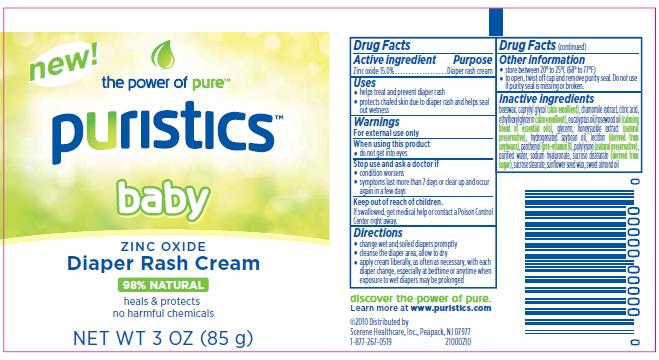 DRUG LABEL: puristics baby zinc oxide diaper rash 
NDC: 76026-200 | Form: CREAM
Manufacturer: Scerene Healthcare, Inc.
Category: otc | Type: HUMAN OTC DRUG LABEL
Date: 20110207

ACTIVE INGREDIENTS: Zinc Oxide 15 g/100 g
INACTIVE INGREDIENTS: Yellow Wax; Caprylyl Glycol; Chamomile; Citric Acid Monohydrate; Ethylhexylglycerin; Eucalyptus Oil; Rosewood Oil; Glycerin; Lonicera Caprifolium Flower; Hydrogenated Soybean Oil; Lecithin, Soybean; Panthenol; Water; Hyaluronate Sodium; Sucrose Stearate; Almond Oil

Diaper Rash Cream

Active Ingredient

Zinc oxide 15.0%

Purpose

Diaper rash cream

Uses

- helps treat and prevent diaper rash
- protects chafed skin due to diaper rash and helps seal out wetness

Warnings

For external use only

When using this product

- do not get into eyes

Stop use and ask a doctor if

- condition worsens
- symptoms last more than 7 days or clear up and occur again in a few days

Keep out of reach of children.

If swallowed, get medical help or contact a Poison Control Center right away.

Directions

- change wet and soiled diapers promptly
- cleanse the diaper area, allow to dry
- apply cream liberally, as often as necessary, with each diaper change, especially at bedtime or anytime when exposure to wet diapers may be prolonged

Other Information

- store between 20° to 25°C (68° to 77°F)
- to open, twist off cap and remove purity seal. Do not use if purity seal is missing or broken.

Inactive Ingredients

beeswax, caprylyl glycol (skin emollient), chamomile extract, citric acid, ethylhexylglycerin (skin emollient), eucalyptus oil/rosewood oil (calming blend of essential oils), glycerin, honeysuckle extract (natural preservative), hydrogenated soybean oil, lecithin (derived from soybeans), panthenol (pro-vitamin B), polylysine (natural preservative), purified water, sodium hyaluronate, sucrose distearate (derived from sugar), sucrose stearate, sunflower seed wax, sweet almond oil

Principal Display Panel

new!

the power of pure™

puristics™

baby

ZINC OXIDE

Diaper Rash Cream

98% NATURAL

heals & protects
no harmful chemicals

NET WT 3 OZ (85 g)

discover the power of pure.
Learn more at www.puristics.com

©2010 Distributed by
Scerene Healthcare, Inc., Peapack, NJ 07977
1-877-267-0519

21000210